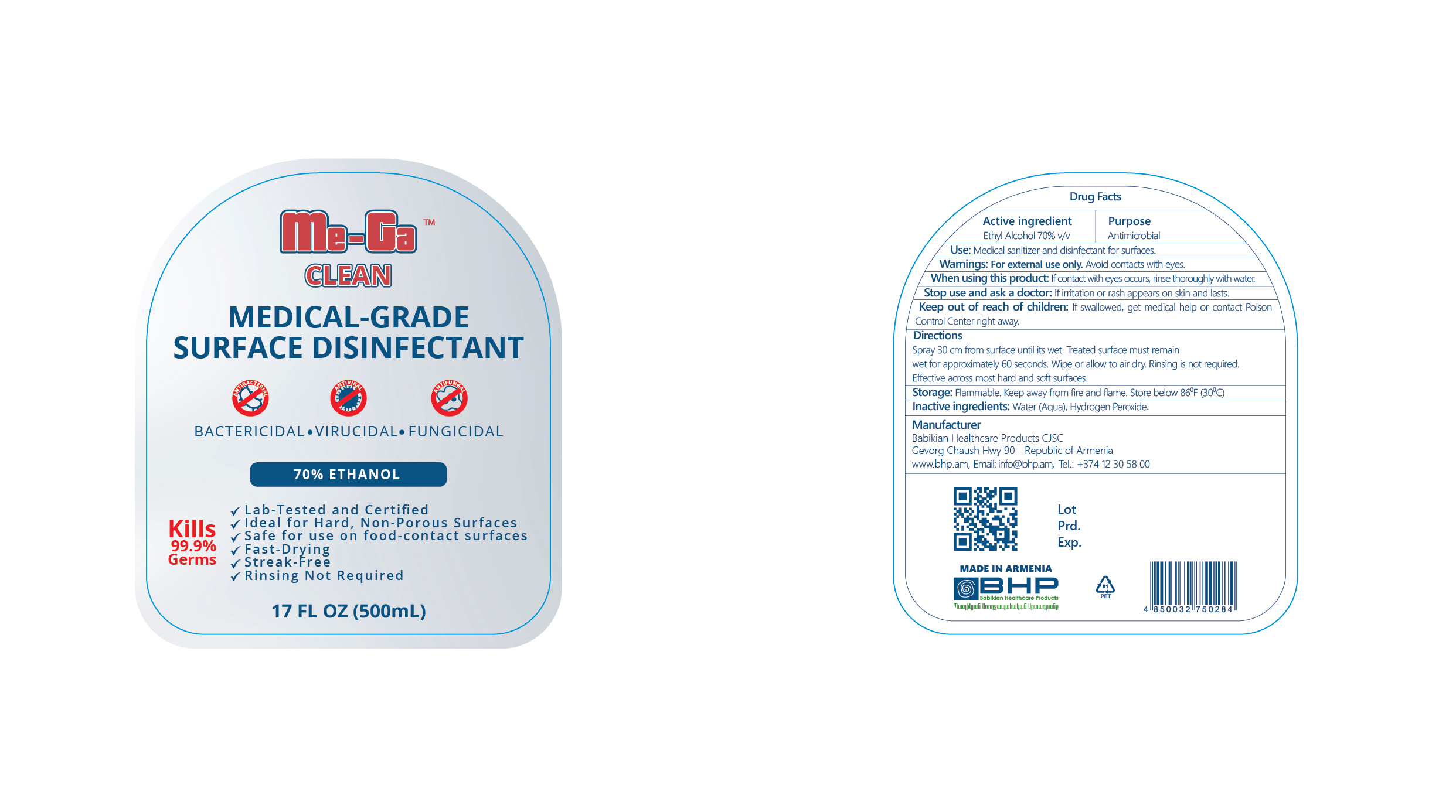 DRUG LABEL: Me-Ga Clean Medical-Grade Surface Disinfectant
NDC: 83640-170 | Form: LIQUID
Manufacturer: Babikian Healthcare Products CJSC
Category: otc | Type: HUMAN OTC DRUG LABEL
Date: 20250508

ACTIVE INGREDIENTS: ALCOHOL 70 mL/100 mL
INACTIVE INGREDIENTS: WATER; HYDROGEN PEROXIDE

Drug Facts

Active ingredients................. Purpose

Ethyl Alcohol 70% v/v ...........Antimicrobial

Use

Medical sanitizer and disinfectant for surfaces

Warnings

For external use only. Avoid contacts with eyes.

When using this product:

If contact with eyes occurs, rinse thoroughly with water.

Stop use and ask a doctor:

If irritation or rash appears on skin and lasts.

Keep out of reach of children:

If swallowed, get medical help or contact Poison Control Center right away.

Directions

Spray 30 cm from surface until its wet. Treated surface must remain wet for approximately 60 seconds. Wipe or allow to air dry. Rinsing is not required. Effective across most hard and soft surfaces.

Storage

Flammable. Keep away from fire and flame. Store below 86⁰F (30⁰C).

Inactive ingredients

Water (Aqua), Hydrogen Peroxide.

QUESTIONS

Manufacturer

Babikian Healthcare Products CJSC

Gevorg Chaush Hwy 90 - Republic of Armenia

www.bhp.am,

Email: info@bhp.am,

Tel.: +374 12 30 58 00